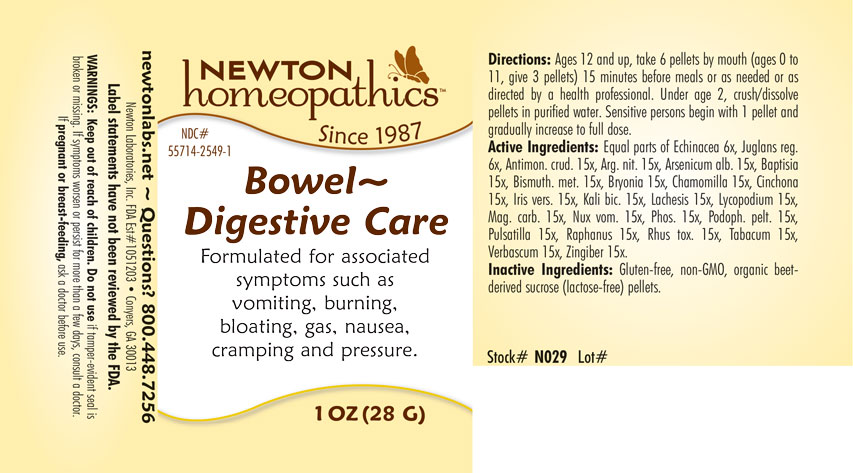 DRUG LABEL: Bowel - Digestive Care
NDC: 55714-2549 | Form: PELLET
Manufacturer: Newton Laboratories, Inc.
Category: homeopathic | Type: HUMAN OTC DRUG LABEL
Date: 20201124

ACTIVE INGREDIENTS: BISMUTH 15 [hp_X]/1 g; ANTIMONY TRISULFIDE 15 [hp_X]/1 g; SILVER NITRATE 15 [hp_X]/1 g; ARSENIC TRIOXIDE 15 [hp_X]/1 g; BAPTISIA TINCTORIA 15 [hp_X]/1 g; BRYONIA ALBA ROOT 15 [hp_X]/1 g; MATRICARIA RECUTITA 15 [hp_X]/1 g; CINCHONA OFFICINALIS BARK 15 [hp_X]/1 g; IRIS VERSICOLOR ROOT 15 [hp_X]/1 g; POTASSIUM DICHROMATE 15 [hp_X]/1 g; LACHESIS MUTA VENOM 15 [hp_X]/1 g; LYCOPODIUM CLAVATUM SPORE 15 [hp_X]/1 g; MAGNESIUM CARBONATE 15 [hp_X]/1 g; STRYCHNOS NUX-VOMICA SEED 15 [hp_M]/1 g; PHOSPHORUS 15 [hp_X]/1 g; PODOPHYLLUM 15 [hp_X]/1 g; PULSATILLA VULGARIS 15 [hp_X]/1 g; RADISH 15 [hp_X]/1 g; TOXICODENDRON PUBESCENS LEAF 15 [hp_X]/1 g; TOBACCO LEAF 15 [hp_X]/1 g; VERBASCUM THAPSUS 15 [hp_X]/1 g; GINGER 15 [hp_X]/1 g; ECHINACEA, UNSPECIFIED 6 [hp_X]/1 g; ENGLISH WALNUT 6 [hp_X]/1 g
INACTIVE INGREDIENTS: SUCROSE

Bowel 2549P

INDICATIONS & USAGE SECTION

Formulated for associated symptoms such as vomiting, burning, bloating, gas, nausea, cramping and pressure.

DOSAGE & ADMINISTRATION SECTION

Directions: Ages 12 and up, take 6 pellets by mouth (ages 0 to 11, give 3 pellets) 15 minutes before meals or as needed or as directed by a health professional. Under age 2, crush/dissolve pellets in purified water. Sensitive persons begin with 1 pellet and gradually increase to full dose.

OTC - ACTIVE INGREDIENT SECTION

Equal parts of Echinacea 6x, Juglans reg. 6x, Antimon.crud. 15x, Arg. nit. 15x, Arsenicum alb. 15x, Baptisia 15x, Bismuth. met. 15x, Bryonia 15x, Chamomilla 15x, Cinchona 15x, Iris versicolor 15x, Kali bic. 15x, Lachesis 15x, Lycopodium 15x, Mag. carb. 15x, Nux vom. 15x, Phosphorus 15x, Podoph. pelt. 15x, Pulsatilla 15x, Raphanus 15x, Rhus toxicodendron 15x, Tabacum 15x, Verbascum 15x, Zingiber 15x.

OTC - PURPOSE SECTION

Formulated for associated symptoms such as vomiting, burning, bloating, gas, nausea, cramping and pressure.

INACTIVE INGREDIENT SECTION

Inactive Ingredients: Gluten-free, non-GMO, organic beet-derived sucrose (lactose-free) pellets.

QUESTIONS SECTION

newtonlabs.net - Questions? 800 448.7256

Newton Laboratories, Inc. FDA Est # 1051203 - Conyers, GA 30013

WARNINGS SECTION

WARNINGS: Keep out of reach of children. Do not use if tamper - evident seal is broken or missing. If symptoms worsen or persist for more then a few days, consult a doctor. If pregnant or breast-feeding, ask a doctor before use.

OTC - PREGNANCY OR BREAST FEEDING SECTION

If pregnant or breast-feeding, ask a doctor before use.

OTC - KEEP OUT OF REACH OF CHILDREN SECTION

Keep out of reach of children.